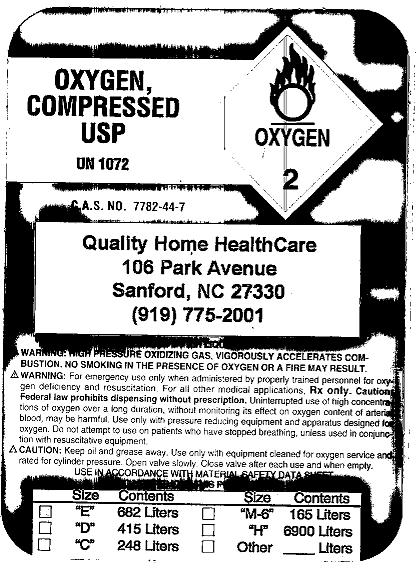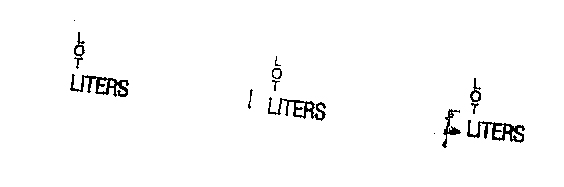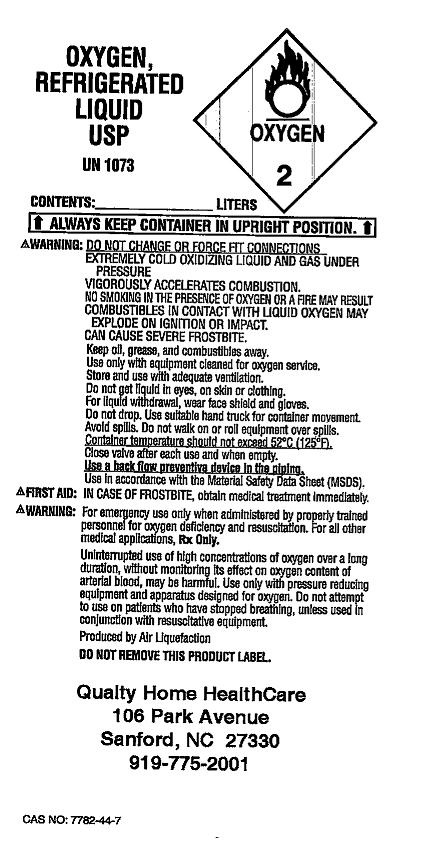 DRUG LABEL: Oxygen
NDC: 61458-0001 | Form: GAS
Manufacturer: Quality Home Healthcare, Inc. 
Category: prescription | Type: HUMAN PRESCRIPTION DRUG LABEL
Date: 20091217

ACTIVE INGREDIENTS: Oxygen 99 L/100 L

Oxygen